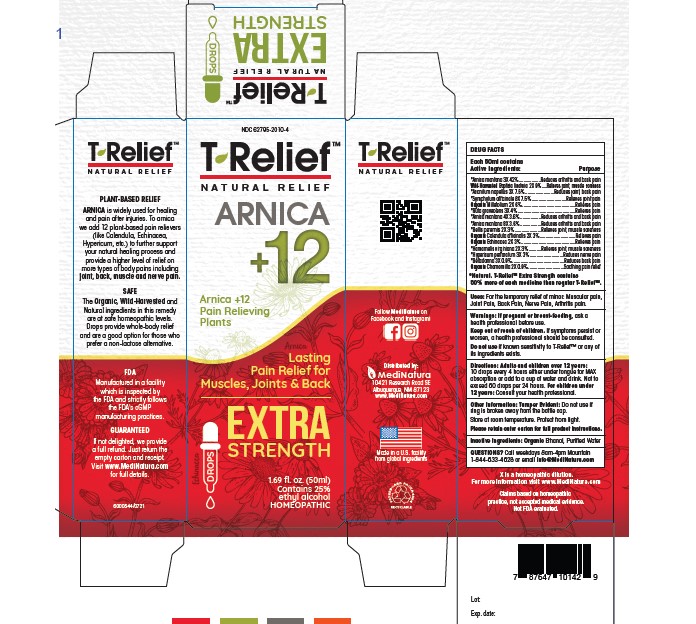 DRUG LABEL: T-Relief Extra Strength
NDC: 62795-2010 | Form: SOLUTION/ DROPS
Manufacturer: MediNatura Inc
Category: homeopathic | Type: HUMAN OTC DRUG LABEL
Date: 20230928

ACTIVE INGREDIENTS: CALENDULA OFFICINALIS FLOWERING TOP 2 [hp_X]/50 mL; MATRICARIA RECUTITA 2 [hp_X]/50 mL; HAMAMELIS VIRGINIANA ROOT BARK/STEM BARK 3 [hp_X]/50 mL; ACHILLEA MILLEFOLIUM 2 [hp_X]/50 mL; RUTA GRAVEOLENS FLOWERING TOP 3 [hp_X]/50 mL; COMFREY ROOT 8 [hp_X]/50 mL; ACONITUM NAPELLUS 3 [hp_X]/50 mL; ECHINACEA, UNSPECIFIED 2 [hp_X]/50 mL; BAPTISIA TINCTORIA ROOT 2 [hp_X]/50 mL; ATROPA BELLADONNA 3 [hp_X]/50 mL; ARNICA MONTANA 3 [hp_X]/50 mL; BELLIS PERENNIS 2 [hp_X]/50 mL; HYPERICUM PERFORATUM 3 [hp_X]/50 mL
INACTIVE INGREDIENTS: WATER; ALCOHOL

T-Relief Extra Strength

WARNINGS

If pregnant or breast-feeding, ask a health professional before use. Keep out of reach of children. If symptoms persist or worsen, a health professional should be consulted . Do not use if known sensitivity to T-Relief TM or any of its ingredients exists.

USES

For the temporary relief of minor: Muscular Pain, Joint Pain, Back Pain, Nerve Pain and Arthritis Pain.

KEEP OUT OF REACH OF CHILDREN

If symptoms persist or worsen, a health professional should be consulted .

PURPOSE

Relieves

• Joint Pain

• Back Pain

• Muscular Pain

Directions

Adults and children 12 years and older: 10 drops every 4 hours either under the tongue for MAX absorption or add to a cup of water and drink. Not exceed 60 drops per 24 hours. For children under 12 years: Consult your health professional.

INACTIVE INGREDIENTS

Ethanol, Purified water

ACTIVE INGREDIENTS

Each 50mL contains: *Arnica montana 3X 42%,
Wild-Harvested Baptisia tinctoria 2X 9%, *Aconitum napellus 3X 7.5%,
*Symphytum officinale 8X 7.5%, Organic Millefolium 2X 6%, *Ruta
graveolens 3X 4%, *Arnica montana 4X 3.6%, *Arnica montana 8X 3.6%,
*Bellis perennis 2X 3%, Organic Calendula officinalis 2X 3%, Organic
Echinacea 2X 3%, *Hamamelis virginiana 2X 3%, *Hypericum perforatum
3X 3%, *Belladonna 3X 0.9%, Organic Chamomilla 2X 0.9%